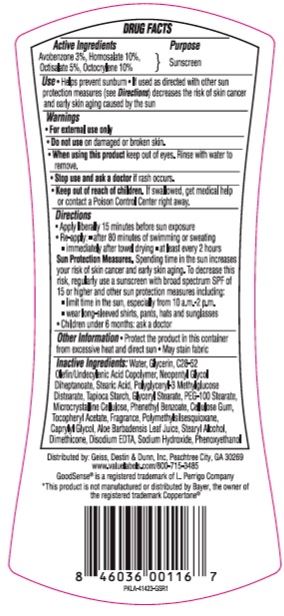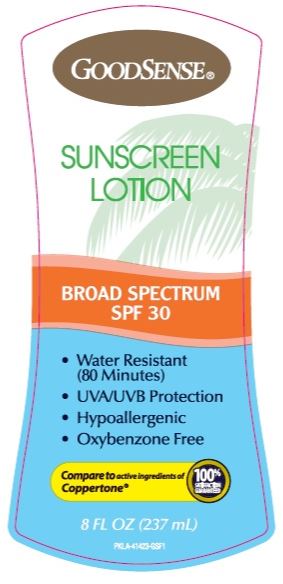 DRUG LABEL: GoodSense Sunscreen SPF 30
NDC: 70281-601 | Form: LOTION
Manufacturer: Solskyn Personal Care LLC
Category: otc | Type: HUMAN OTC DRUG LABEL
Date: 20190627

ACTIVE INGREDIENTS: OCTISALATE 5 g/100 g; AVOBENZONE 3 g/100 g; HOMOSALATE 10 g/100 g; OCTOCRYLENE 10 g/100 g
INACTIVE INGREDIENTS: POLYMETHYLSILSESQUIOXANE (4.5 MICRONS); ALOE VERA LEAF; DIMETHICONE; WATER; GLYCERIN; STEARIC ACID; NEOPENTYL GLYCOL DIHEPTANOATE; POLYGLYCERIN-3; METHYL GLUCOSE; STARCH, TAPIOCA; GLYCERYL STEARATE SE; CELLULOSE, MICROCRYSTALLINE; PEG-100 STEARATE; PHENETHYL BENZOATE; CARBOXYMETHYLCELLULOSE; .ALPHA.-TOCOPHEROL ACETATE; CAPRYLYL GLYCOL; STEARYL ALCOHOL; EDETATE DISODIUM; SODIUM HYDROXIDE; PHENOXYETHANOL

GoodSense Sunscreen SPF 30

Active Ingredients

Avebenzone 3%,

Homosalate 10%

Octisalate 5%,

Octocrylene 10%

Purpose

Sunscreen

Warnings

For external use only.

Do not use on damaged or broken skin.

Stop use and ask a doctor if rash occurs.

Keep out of reach of children. If swallowed, get medical help or contact a Poison Control Center right away.

Directions

- Apply liberally 15 minutes before sun exposure
- Re-apply
  - after 80 minutes of swimming or sweating
  - Immediately after towel drying
  - at least every 2 hours
- DFD

Sun Protection Measures. Spending time in the sun increases your risk of skin cancer and early skin aging. To decrease this risk, regularly use a sunscreen with broad spectrum SPF of 15 or higher and other sun protection measures including:

- limit time in the sun, especially from 10a.m.-2p.m.
- war long-sleeved shirt, pants, hats, and sunglasses
- Children under 6 months: ask a doctor

Other information

- Protect the product in this container from excessive heat and direct sun.
- May stain fabric

Inactive ingredients

Inactive ingredients: Water, Glycerin, C28-52 Olefin/Undecylenic Acid Copolymer, Neopentyl Glycol, Diheptanoate, Stearic Acid, Polyglyceryl-3, Methylglucose, Distearate, Tapioca Starch, Glyceryl Stearate, PEG-100 Stearate, Microcrystalline Cellulose, Phenethyl Benzoate, Cellulose Gum, Tocopheryl Acetate, Fragrance, Polymethylsilsesquioxane, Caprylyl Glycol, Aloe Barbadensis Leaf Juice, Stearyl Alcohol, Dimethicone, Disodium EDTA, Sodium Hydroxide, Phenoxyethanol

Distributed by

Distributed by: Geiss, Destin & Dunn, Inc, Peachtree City, GA 30269
www.valuelabels.com/800-715-3485
GoodSense® is a registered trademark of L. Perrigo Company
*This product is not manufactured or distributed by Bayer, the owner of
the registered trademark Coppertone®

Principal Display Panel

GOODSENSE

SUNSCREEN

LOTION

BROAD SPECTRUM

SPF 30

- Water Resistant

(80 Minutes)

- UVA/UVB Protection
- Hypoallergenic
- Oxybenzone Free

Compare to active ingredients of

Coppertone

100%

Satisfaction

Guaranteed

8 FL OZ (237 mL)

PKLA-41423-GSF1